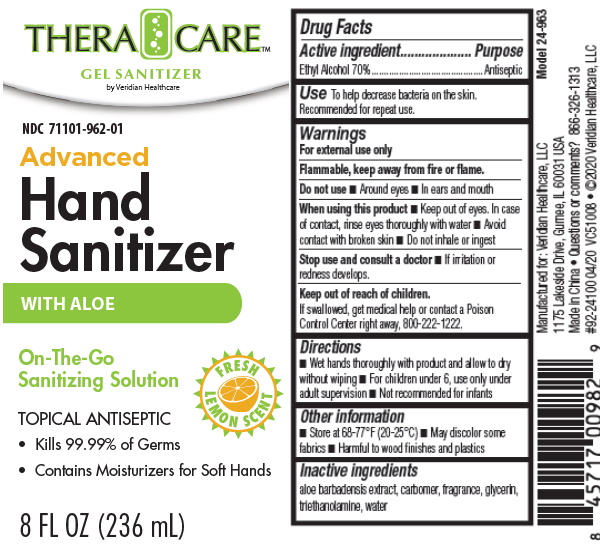 DRUG LABEL: ADVANCE HAND SANITIZER WITH ALOE
NDC: 71101-962 | Form: GEL
Manufacturer: Veridian Healthcare
Category: otc | Type: HUMAN OTC DRUG LABEL
Date: 20200101

ACTIVE INGREDIENTS: ALCOHOL 70 mL/100 mL
INACTIVE INGREDIENTS: WATER; CARBOMER 980; GLYCERIN; ISOPROPYL MYRISTATE; ALOE VERA LEAF; TRIETHANOLAMINE BENZOATE

Active ingredient

Ethyl Alcohol 70.0%

Purpose

Antimicrobial

Uses

To help decrease bacteria on the skin. Recommended for repeat use.

Warnings

For external use only.

WARNINGS

Flammable. Keep away from heat and flame.

When using this product

• Keep out of eyes. In case of contact, rinse eyes thoroughly with water

• Avoid contact with broken skin

• Do not inhale or ingest

Stop use and ask a doctor if

If irritation or redness develops.

Keep out of reach of children.

If swallowed, get medical help or contact a Poison Control Center right away 800-222-1222.

Directions

• Wet hands thoroughly with product and allow to dry without wiping
• For children under 6, use only under adult supervision
• Not recommended for infants

Inactive ingredients

aloe barbadensis extract, carbomer, fragrance, glycerin,
triethanolamine, water